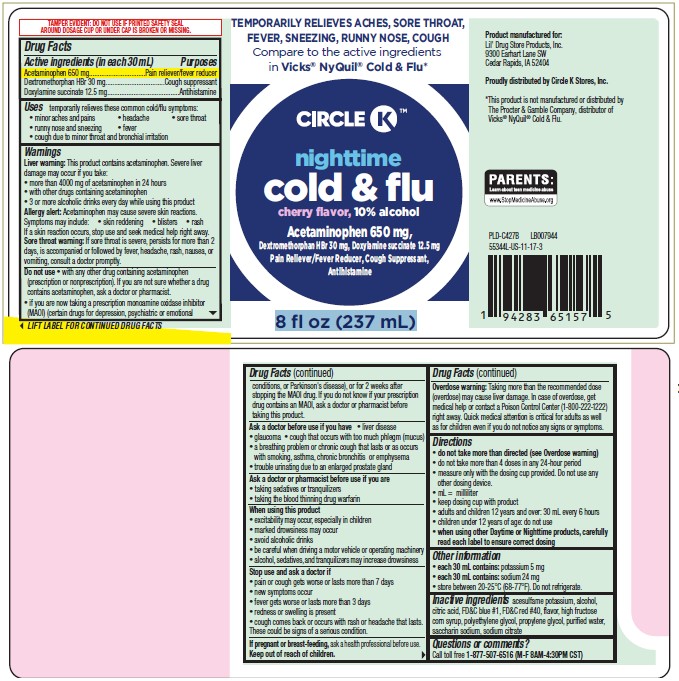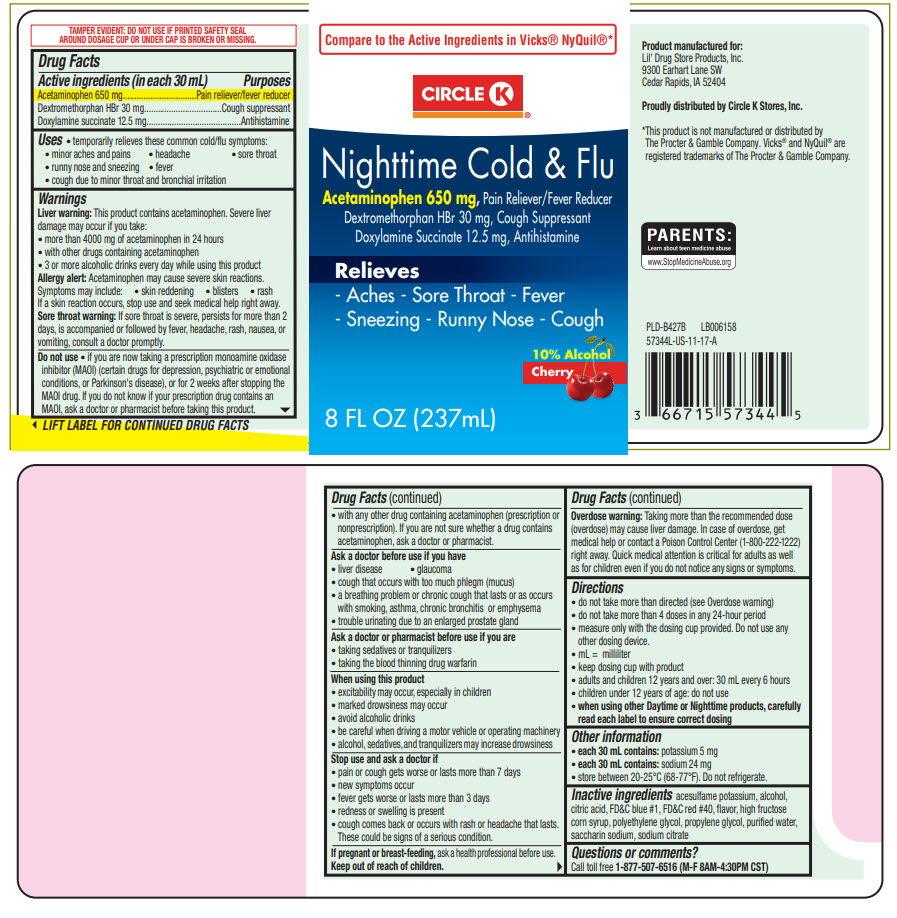 DRUG LABEL: Circle K Nighttime Cold and Flu
NDC: 66715-5534 | Form: LIQUID
Manufacturer: Lil' Drug Store Products, Inc
Category: otc | Type: HUMAN OTC DRUG LABEL
Date: 20251209

ACTIVE INGREDIENTS: ACETAMINOPHEN 650 mg/30 mL; DEXTROMETHORPHAN HYDROBROMIDE 30 mg/30 mL; DOXYLAMINE SUCCINATE 12.5 mg/30 mL
INACTIVE INGREDIENTS: ACESULFAME POTASSIUM; ALCOHOL; CITRIC ACID MONOHYDRATE; FD&C BLUE NO. 1; FD&C RED NO. 40; HIGH FRUCTOSE CORN SYRUP; POLYETHYLENE GLYCOL, UNSPECIFIED; PROPYLENE GLYCOL; WATER; SACCHARIN SODIUM; SODIUM CITRATE, UNSPECIFIED FORM

Circle K™ Nighttime Cold & Flu

Drug Facts

ACTIVE INGREDIENT

PURPOSE

Active ingredients (in each 30 mL) | Purposes
Acetaminophen 650 mg | Pain reliever/fever reducer
Dextromethorphan HBr 30 mg | Cough suppressant
Doxylamine succinate 12.5 mg | Antihistamine

Uses

- temporarily relieves these common cold/flu symptoms:
  - minor aches and pains
  - headache
  - sore throat
  - runny nose and sneezing
  - fever
  - cough due to minor throat and bronchial irritation

Warnings

Liver warning

This product contains acetaminophen. Severe liver damage may occur if you take:

- more than 4000 mg of acetaminophen in 24 hours
- with other drugs containing acetaminophen
- 3 or more alcoholic drinks every day while using this product

Allergy alert

Acetaminophen may cause severe skin reactions. Symptoms may include:

- skin reddening
- blisters
- rash

If a skin reaction occurs, stop use and seek medical help right away.

Sore throat warning

If sore throat is severe, persists for more than 2 days, is accompanied or followed by fever, headache, rash, nausea, or vomiting, consult a doctor promptly.

Do not use

- if you are now taking a prescription monoamine oxidase inhibitor (MAOI) (certain drugs for depression, psychiatric or emotional conditions, or Parkinson's disease), or for 2 weeks after stopping the MAOI drug. If you do not know if your prescription drug contains an MAOI, ask a doctor or pharmacist before taking this product.
- with any other drug containing acetaminophen (prescription or nonprescription). If you are not sure whether a drug contains acetaminophen, ask a doctor or pharmacist.

Ask a doctor before use if you have

- liver disease
- glaucoma
- cough that occurs with too much phlegm (mucus)
- a breathing problem or chronic cough that lasts or as occurs with smoking, asthma, chronic bronchitis or emphysema
- trouble urinating due to an enlarged prostate gland

Ask a doctor or pharmacist before use if you are

- taking sedatives or tranquilizers
- taking the blood thinning drug warfarin

When using this product

- excitability may occur, especially in children
- marked drowsiness may occur
- avoid alcoholic drinks
- be careful when driving a motor vehicle or operating machinery
- alcohol, sedatives, and tranquilizers may increase drowsiness

Stop use and ask a doctor if

- pain or cough gets worse or lasts more than 7 days
- new symptoms occur
- fever gets worse or lasts more than 3 days
- redness or swelling is present
- cough comes back or occurs with rash or headache that lasts.
  These could be signs of a serious condition.

PREGNANCY OR BREAST FEEDING

If pregnant or breast-feeding, ask a health professional before use.

Keep out of reach of children.

Overdose warning

Taking more than the recommended dose (overdose) may cause liver damage. In case of overdose, get medical help or contact a Poison Control Center (1-800-222-1222) right away. Quick medical attention is critical for adults as well as for children even if you do not notice any signs or symptoms.

Directions

- do not take more than directed (see Overdose warning)
- do not take more than 6 doses in any 24-hour period
- measure only with the dosing cup provided. Do not use any other dosing device.
- mL = milliliter
- keep dosing cup with product
- adults and children 12 years and over: 30 mL every 6 hours
- children under 12 years of age: do not use
- when using other Daytime or Nighttime products, carefully read each label to ensure correct dosing

Other information

- each 30 mL contains: potassium 5 mg
- each 30 mL contains: sodium 24 mg
- store between 20-25°C (68-77°F). Do not refrigerate.

Inactive ingredients

acesulfame potassium, alcohol, citric acid, FD&C blue #1, FD&C red #40, flavor, high fructose corn syrup, polyethylene glycol, propylene glycol, purified water, saccharin sodium, sodium citrate

Questions or comments?

Call toll free 1-877-507-6516 (M-F 8AM-4:30PM CST)

Proudly distributed by Circle K Stores Inc.

PRINCIPAL DISPLAY PANEL - 237 mL Bottle Label

Compare to the Active Ingredients in Vicks® NyQuil®*

CIRCLE K™

Nighttime Cold & Flu

Acetaminophen 650 mg, Pain Reliever/Fever Reducer
Dextromethorphan HBr 30 mg, Cough Suppressant
Doxylamine Succinate 12.5 mg, Antihistamine

Relieves

- Aches - Sore Throat - Fever
- Sneezing - Runny Nose - Cough

10% Alcohol
Cherry

8 FL OZ (237mL)

PDP

TEMPORARILY RELIEVES ACHES, SORE THROAT,
FEVER, SNEEZING, RUNNY NOSE, COUGH
Compare to the active ingredients
in Vicks® NyQuil® Cold & Flu*

CIRCLE K

nighttime
cold & flu
cherry flavor, 10% alcohol
Acetaminophen 650 mg,
Dextromethorphan HBr 30 mg, Doxylamine succinate 12.5 mg
Pain Reliever/Fever Reducer, Cough Suppressant,
Antihistamine

8 fl oz (237 mL)